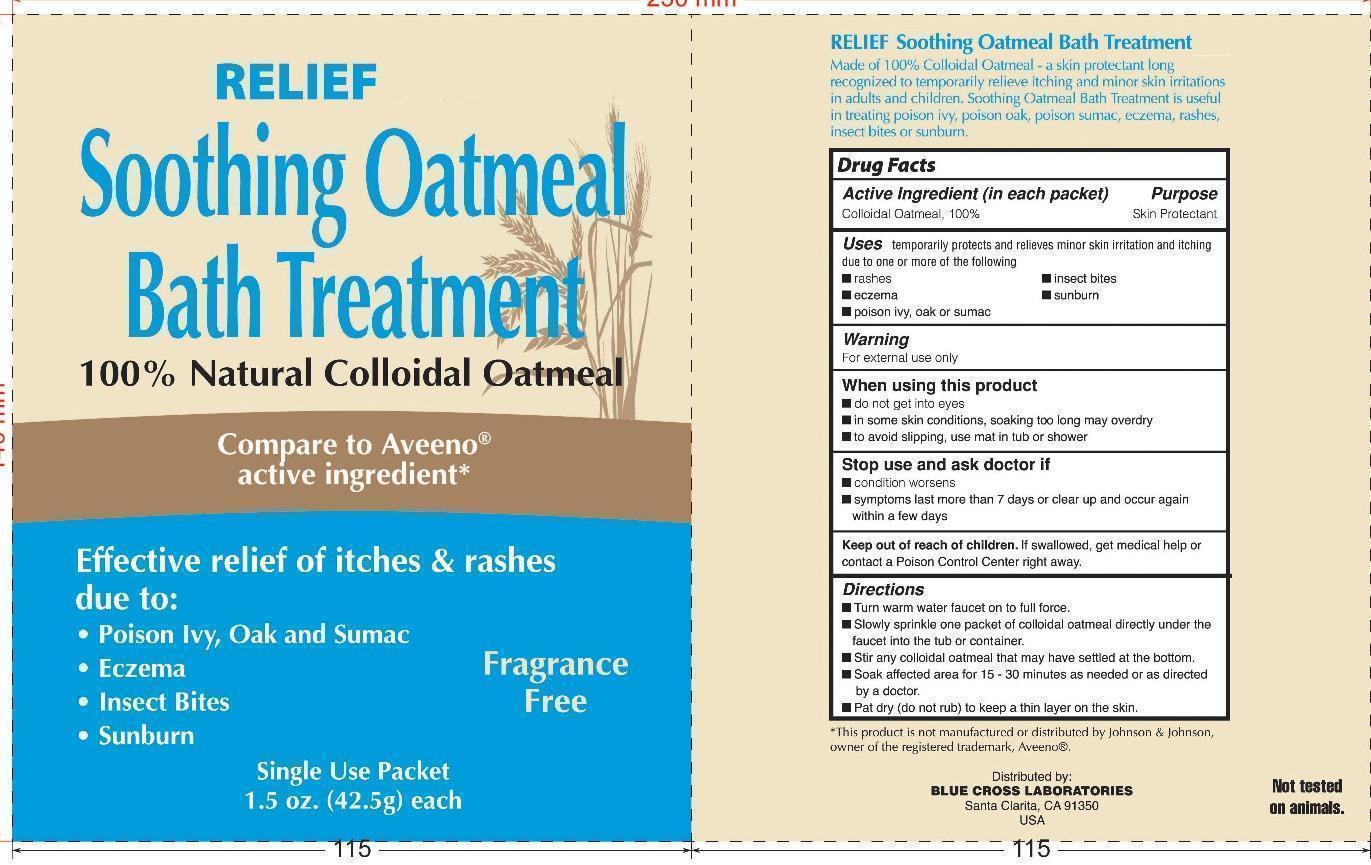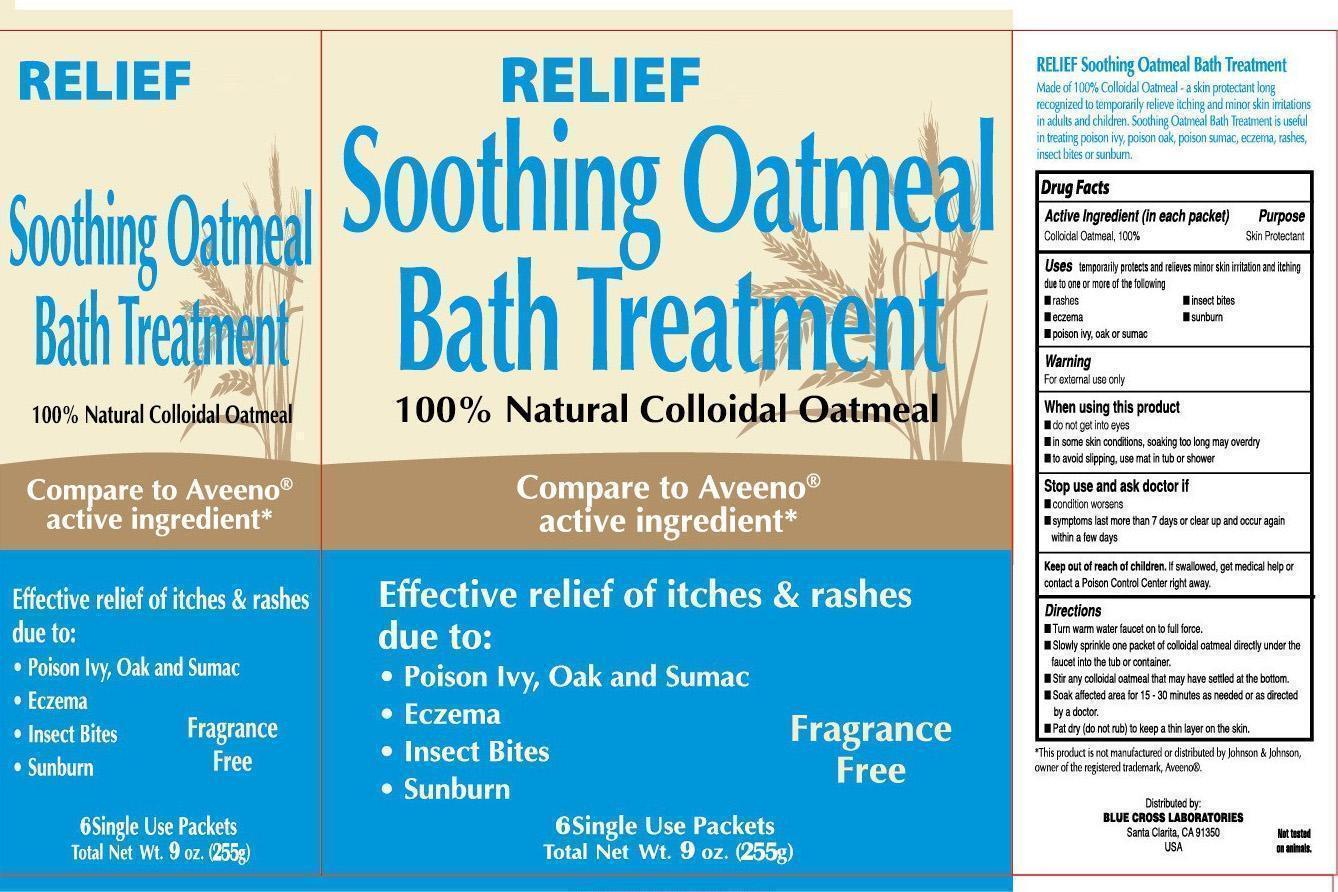 DRUG LABEL: Relief Soothing Bath Treatment
NDC: 22431-359 | Form: GRANULE, EFFERVESCENT
Manufacturer: Blue Cross Laboratories, Inc.
Category: otc | Type: HUMAN OTC DRUG LABEL
Date: 20221115

ACTIVE INGREDIENTS: OATMEAL 1 g/1 g

Soothing Bath Treatment

Active Ingredient (in each packet) Purpose

colloidal oatmeal, 100% Skin protectant

PURPOSE

Uses Temporarily protects and relieves minor skin irritation and itching due to one or more of the following

rashes

eczema

insect bites

sunburn

poison ivy, oak, or sumac

Keep out of reach of children. If swallowed, get medical help or contact a poison Control Center right away.

When using this product

do not get into eyes

in some skin conditions, soaking too long may overdry

to avoid slipping, use mat in tub or shower

WARNINGS

Warning For external use only

Directions
Turn warm water faucet on to full force.
Slowly sprinkle one packet of colloidal oatmeal directly into tub or container.
stir any colloidal oatmeal that may have settled at the bottom.
soak affected area for 15-30 minutes as needed or as directed by a doctor.
pat dry (do not rub) to keep a thin layer on the skin.

No inactive ingredients

PACKAGE LABEL

Relief

Soothing Bath Treatment

6 single use packets

Total net Wt. 9 oz. (255g)